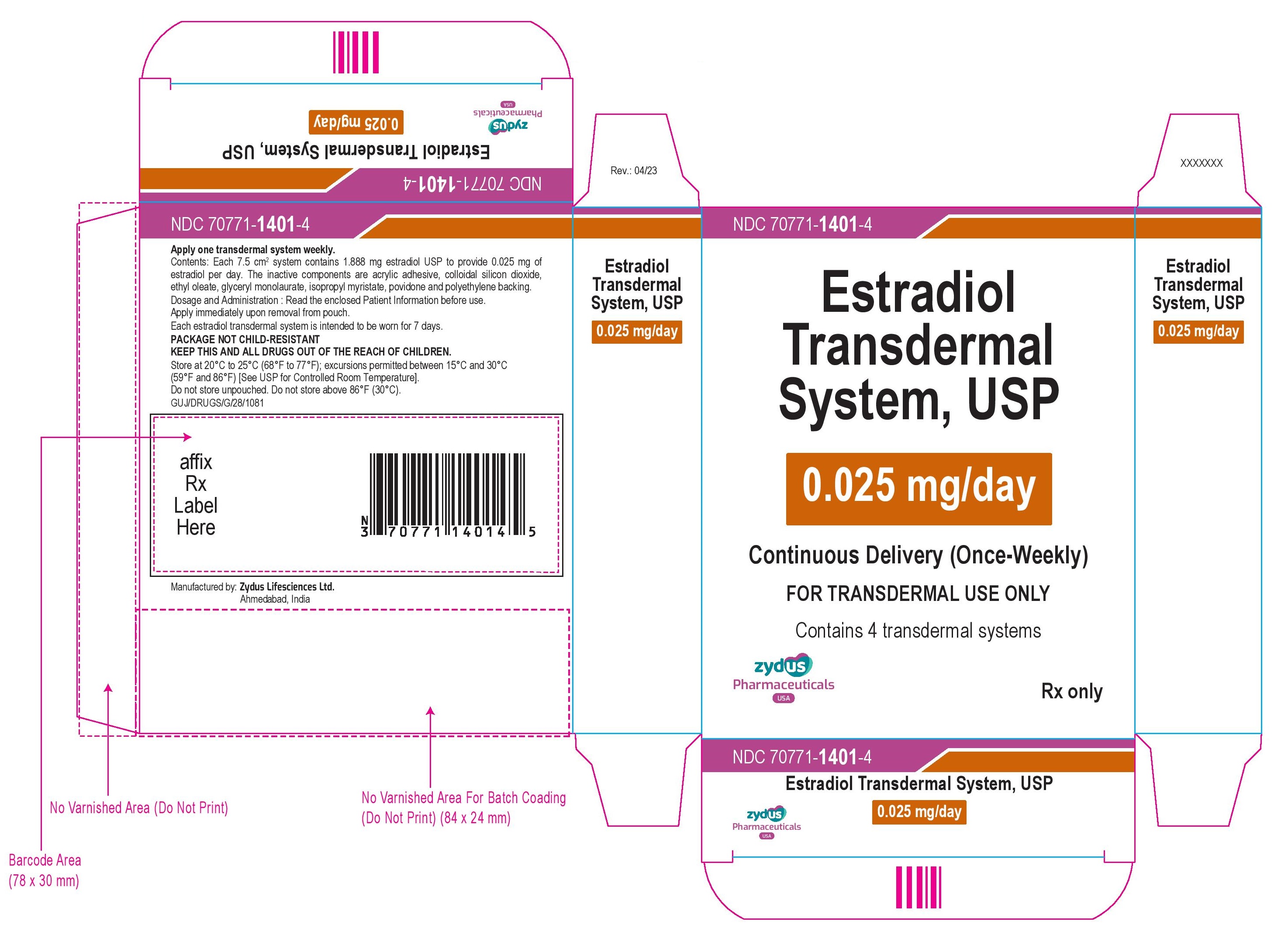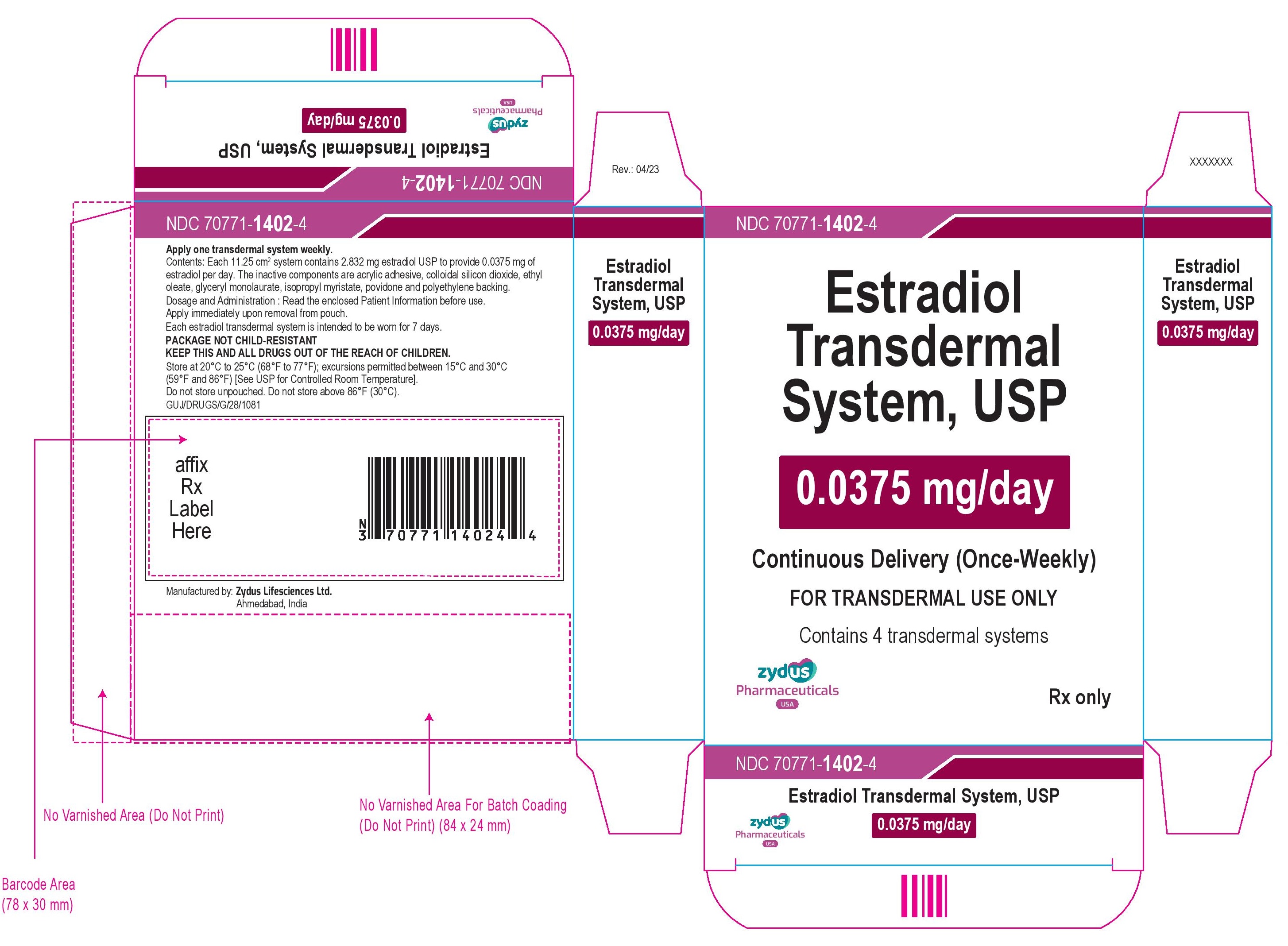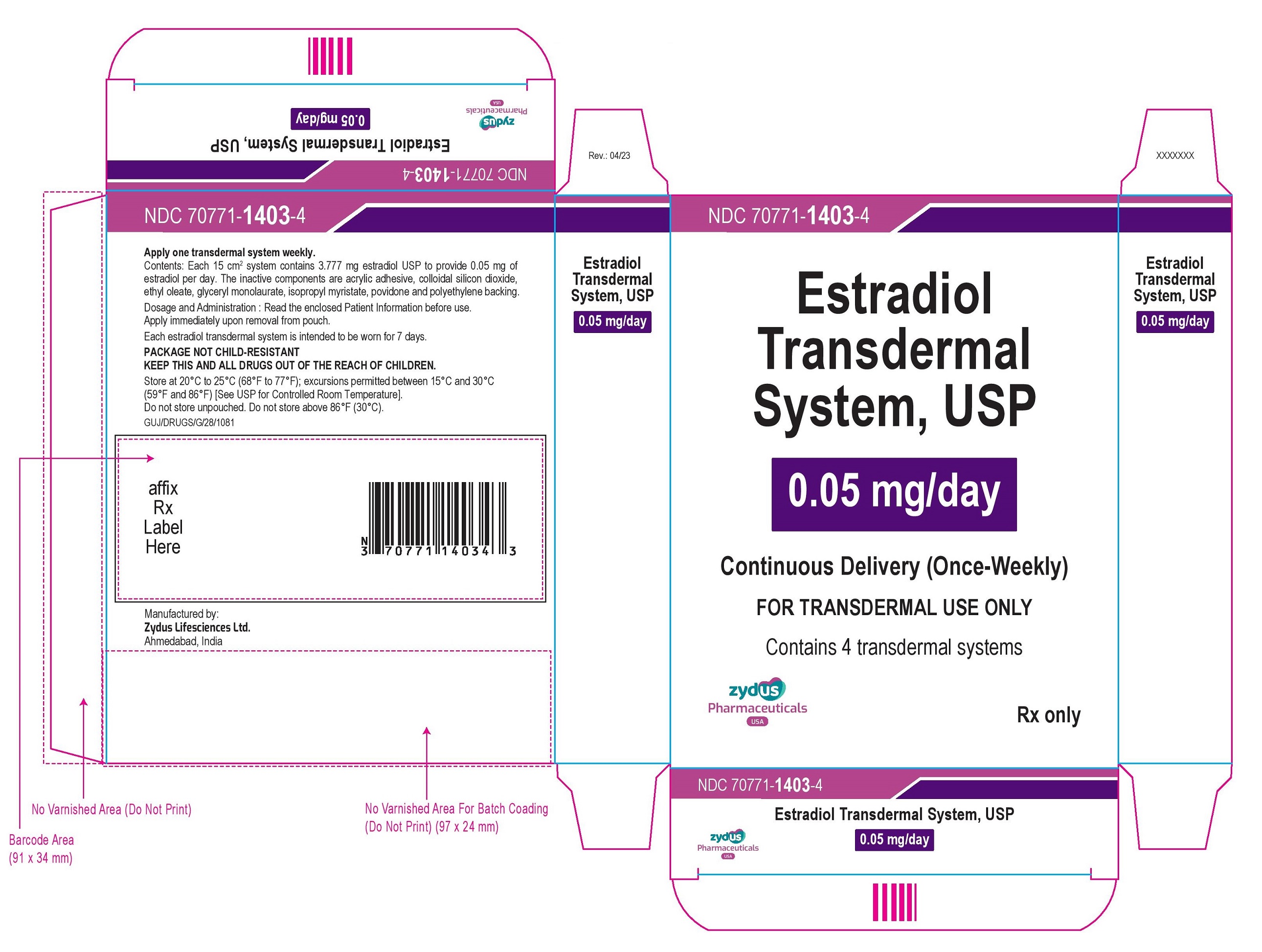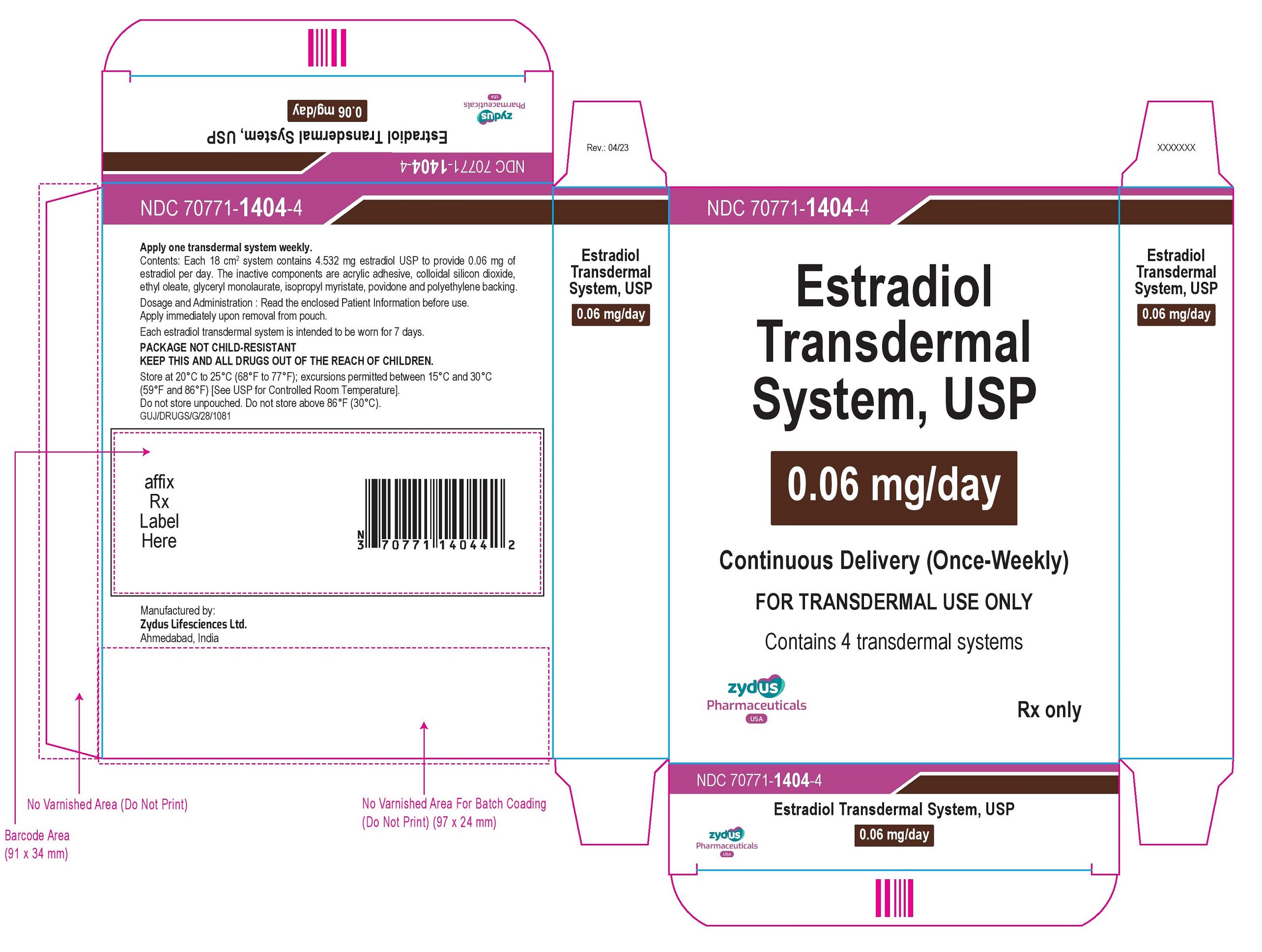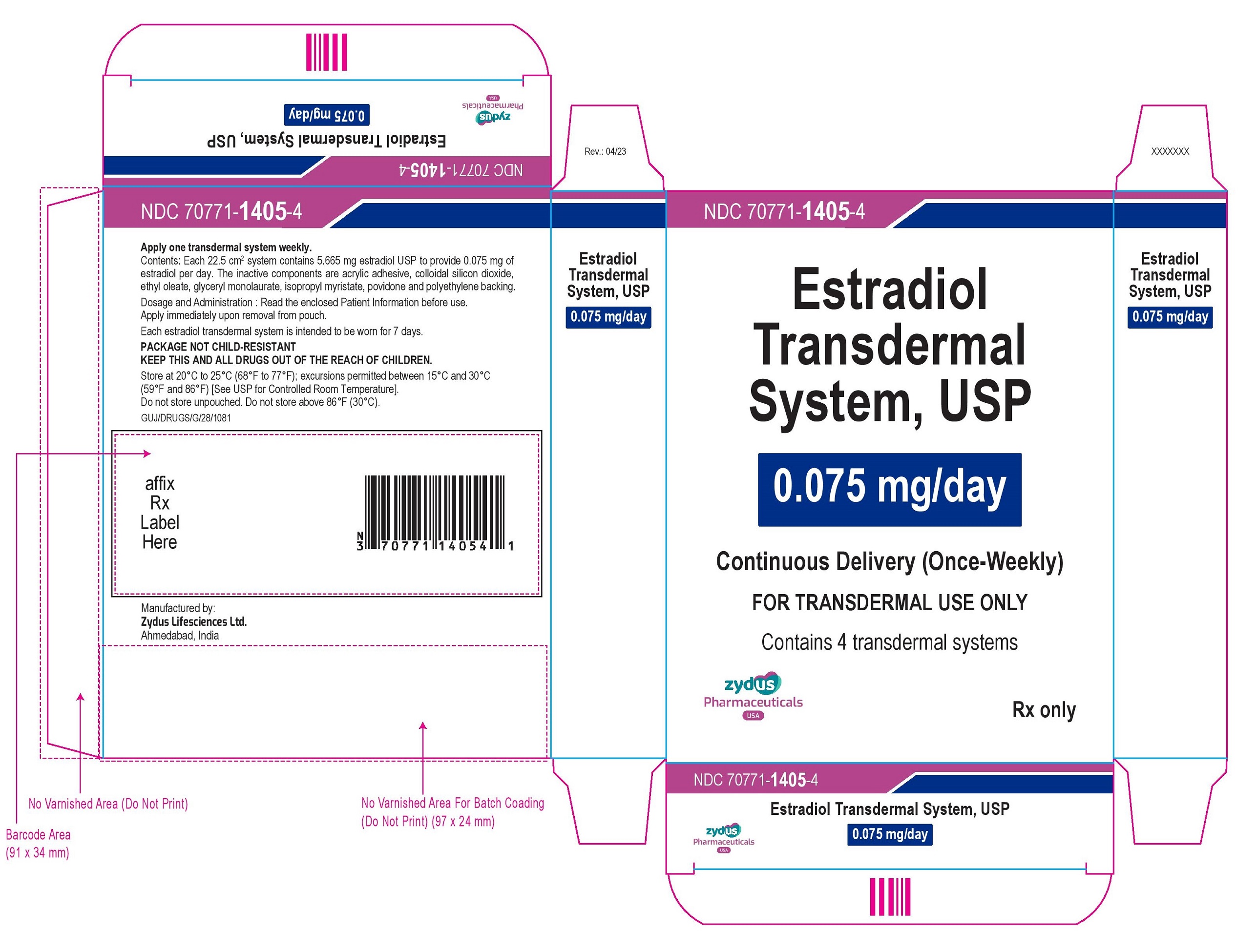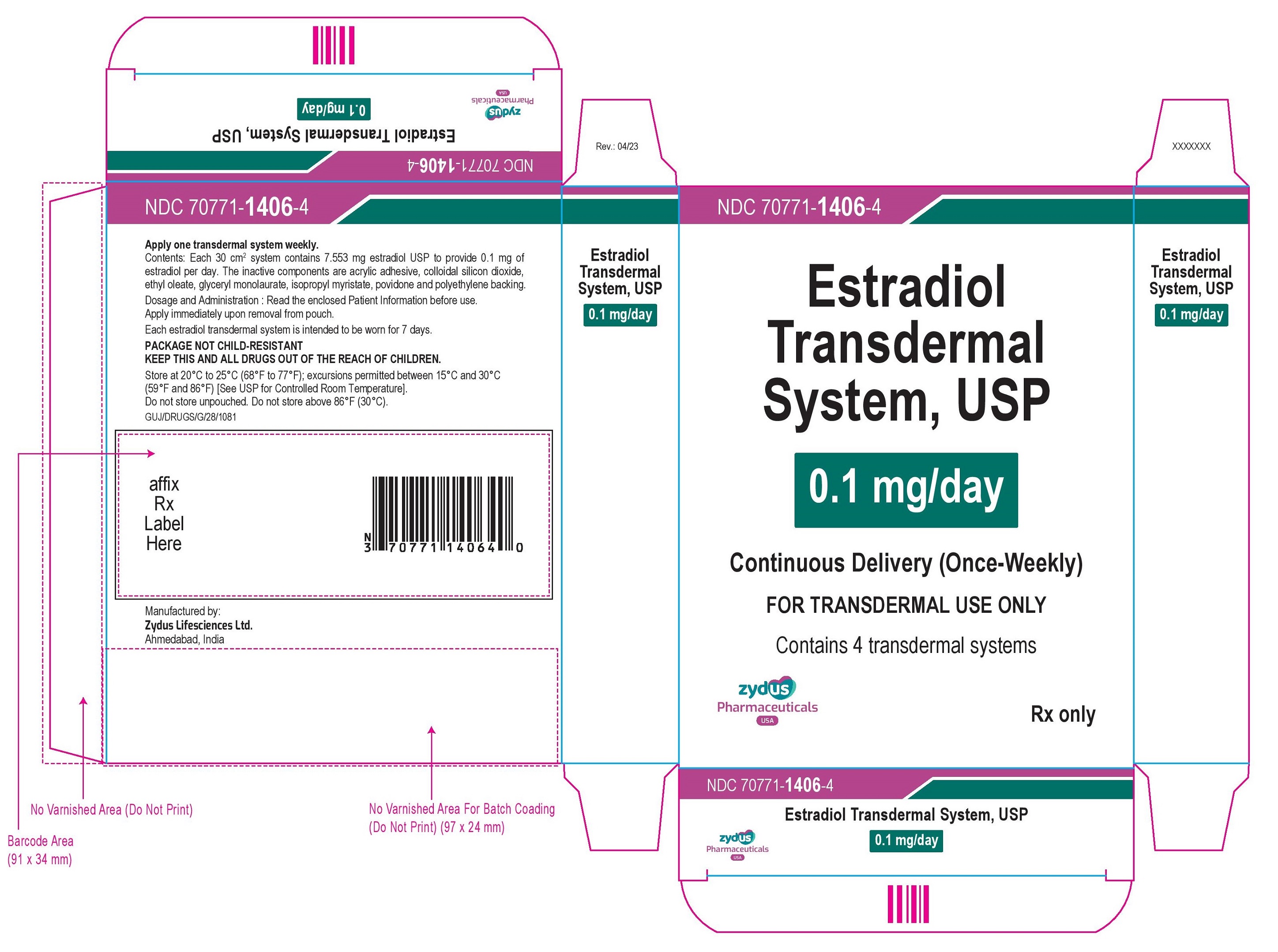 DRUG LABEL: estradiol
NDC: 70771-1401 | Form: PATCH
Manufacturer: Zydus Lifesciences Limited
Category: prescription | Type: HUMAN PRESCRIPTION DRUG LABEL
Date: 20230421

ACTIVE INGREDIENTS: ESTRADIOL 0.025 mg/1 d
INACTIVE INGREDIENTS: 2-ETHYLHEXYL ACRYLATE; 2-HYDROXYETHYL ACRYLATE; ETHYL OLEATE; GLYCERYL LAURATE; GLYCIDYL METHACRYLATE; ISOPROPYL MYRISTATE; POVIDONE; SILICON DIOXIDE; VINYL ACETATE

ESTRADIOL transdermal system

PACKAGE LABEL.PRINCIPAL DISPLAY PANEL

NDC 70771-1401-4

Estradiol Transdermal System, USP

0.025 mg/day

Continuous Delivery (Once-Weekly)

FOR TRANSDERMAL USE ONLY

Contains 4 transdermal systems

Rx only

zydus Pharmaceuticals USA

NDC 70771-1402-4

Estradiol Transdermal System, USP

0.0375 mg/day

Continuous Delivery (Once-Weekly)

FOR TRANSDERMAL USE ONLY

Contains 4 transdermal systems

Rx only

zydus Pharmaceuticals USA

NDC 70771-1403-4

Estradiol Transdermal System, USP

0.05 mg/day

Continuous Delivery (Once-Weekly)

FOR TRANSDERMAL USE ONLY

Contains 4 transdermal systems

Rx only

zydus Pharmaceuticals USA

NDC 70771-1404-4

Estradiol Transdermal System, USP

0.06 mg/day

Continuous Delivery (Once-Weekly)

FOR TRANSDERMAL USE ONLY

Contains 4 transdermal systems

Rx only

zydus Pharmaceuticals USA

NDC 70771-1405-4

Estradiol Transdermal System, USP

0.075 mg/day

Continuous Delivery (Once-Weekly)

FOR TRANSDERMAL USE ONLY

Contains 4 transdermal systems

Rx only

zydus Pharmaceuticals USA

NDC 70771-1406-4

Estradiol Transdermal System, USP

0.1 mg/day

Continuous Delivery (Once-Weekly)

FOR TRANSDERMAL USE ONLY

Contains 4 transdermal systems

Rx only

zydus Pharmaceuticals USA